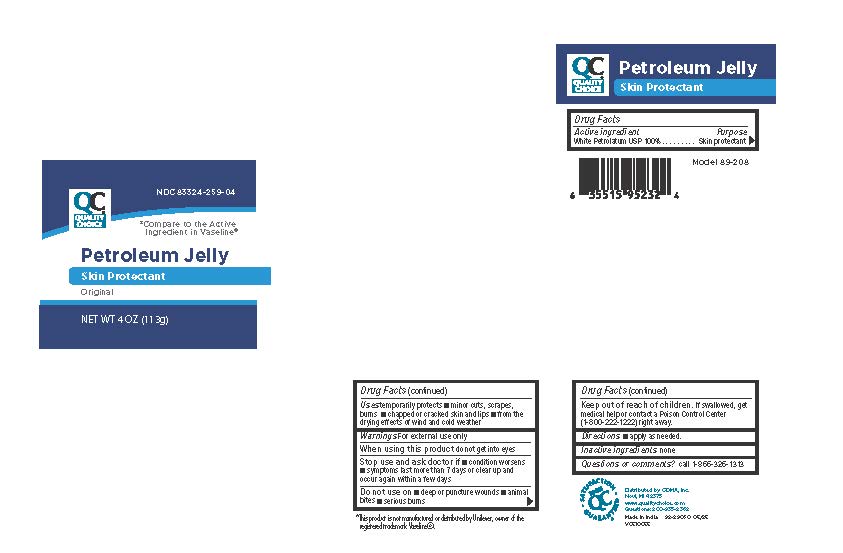 DRUG LABEL: Petroleum
NDC: 83324-259 | Form: JELLY
Manufacturer: QUALITY CHOICE (Chain Drug Marketing Association)
Category: otc | Type: HUMAN OTC DRUG LABEL
Date: 20251112

ACTIVE INGREDIENTS: PETROLATUM 100 g/100 g
INACTIVE INGREDIENTS: WATER

Quality Choice Petrolatum Jelly

Warning

For External Use Only

When using this product do not get into eyes

Active Ingredient

Name Purpose

White Petrolatum 100% USP .............................. Skin Protectant

Inactive Ingredient

Water

Purpose

Skin Protectant

Keep out of the reach of children

If swallowed, get medical help or contact a Poison Control Center (1-800-222-1222)right away

Uses

Temporarily Protects:

minor cuts, scrapes, burns and helps relieve chapped or cracked skin and lips from the drying effects of wind and cold weather

Dosage

Applied as needed.

Stop use and ask doctor if

■ condition worsens

■ symptoms last more than 7 days or clear up and occur again within a few days

Do not use on

■ deep or puncture wounds
■ animal bites

■ serious burns